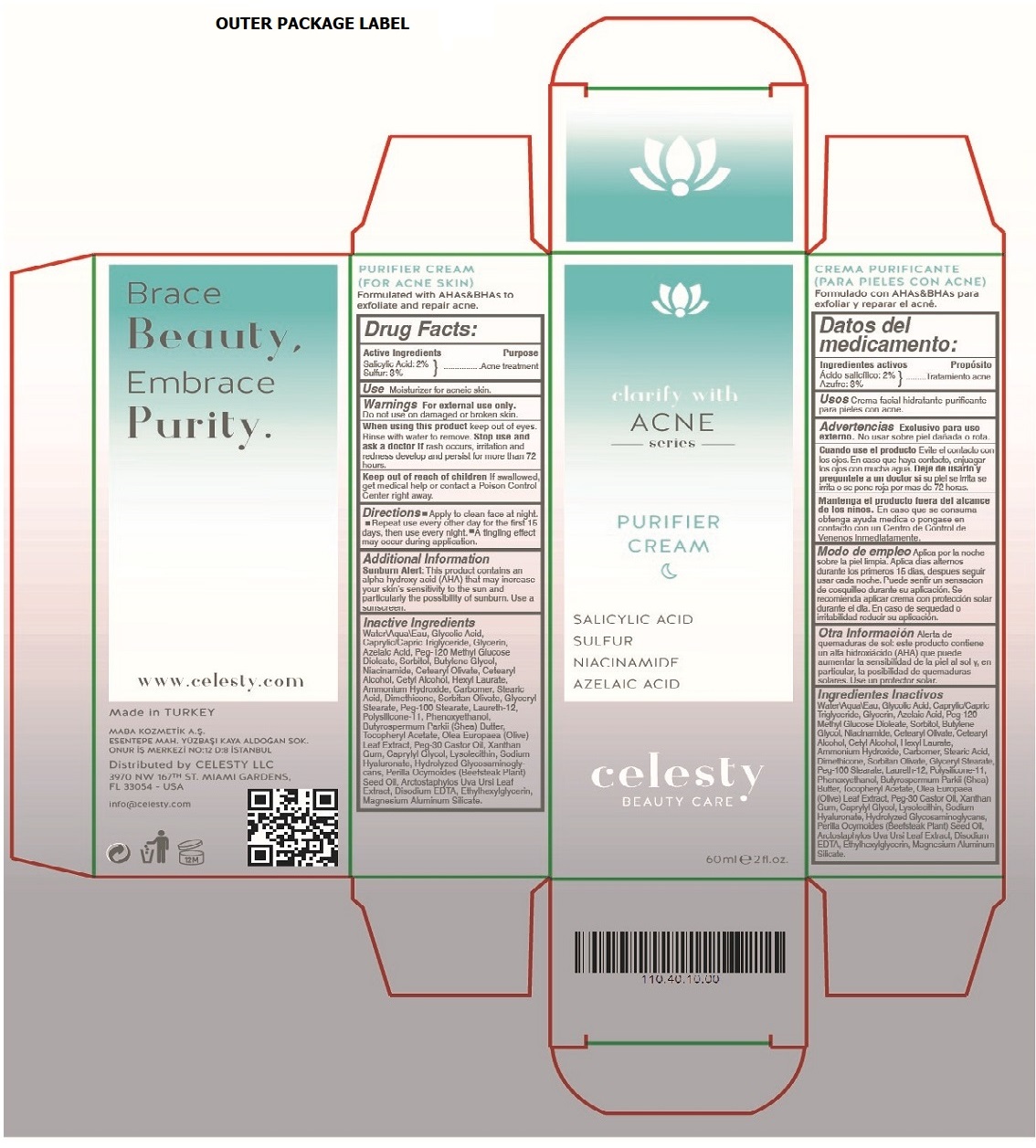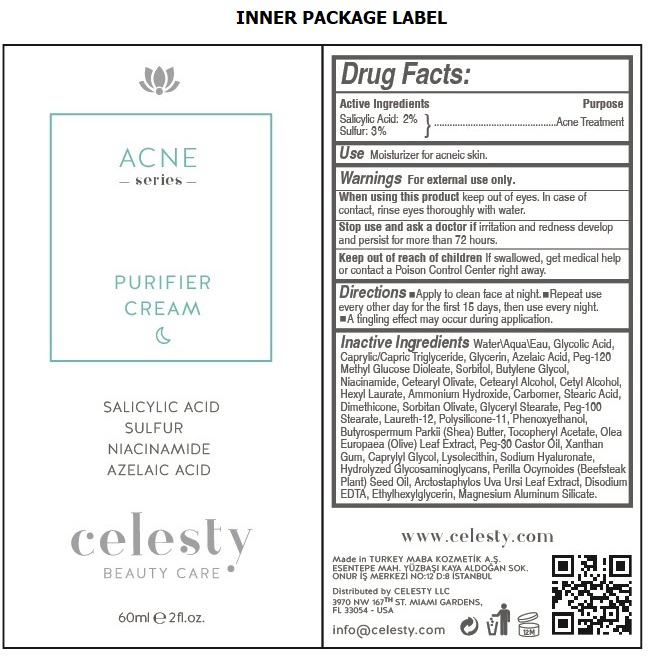 DRUG LABEL: Celesty
NDC: 81120-104 | Form: CREAM
Manufacturer: MABA KOZMETIK LIMITED SIRKETI
Category: otc | Type: HUMAN OTC DRUG LABEL
Date: 20201208

ACTIVE INGREDIENTS: SALICYLIC ACID 20 mg/1 mL; SULFUR 30 mg/1 mL
INACTIVE INGREDIENTS: WATER; GLYCOLIC ACID; MEDIUM-CHAIN TRIGLYCERIDES; GLYCERIN; AZELAIC ACID; PEG-120 METHYL GLUCOSE DIOLEATE; SORBITOL; BUTYLENE GLYCOL; NIACINAMIDE; CETEARYL OLIVATE; CETOSTEARYL ALCOHOL; CETYL ALCOHOL; HEXYL LAURATE; AMMONIA; CARBOMER HOMOPOLYMER, UNSPECIFIED TYPE; STEARIC ACID; DIMETHICONE; SORBITAN OLIVATE; GLYCERYL MONOSTEARATE; PEG-100 STEARATE; LAURETH-12; DIMETHICONE/VINYL DIMETHICONE CROSSPOLYMER (SOFT PARTICLE); PHENOXYETHANOL; SHEA BUTTER; .ALPHA.-TOCOPHEROL ACETATE; OLEA EUROPAEA LEAF; PEG-30 CASTOR OIL; XANTHAN GUM; CAPRYLYL GLYCOL; LYSOPHOSPHATIDYLCHOLINE, SOYBEAN; HYALURONATE SODIUM; HYDROLYZED GLYCOSAMINOGLYCANS (BOVINE; 50000 MW); PERILLA FRUTESCENS SEED OIL; ARCTOSTAPHYLOS UVA-URSI LEAF; EDETATE DISODIUM ANHYDROUS; ETHYLHEXYLGLYCERIN; MAGNESIUM ALUMINUM SILICATE

celesty ACNE series PURIFIER CREAM

Active Ingredients

Salicylic Acid : 2%

Sulfur : 3%

Purpose

Acne treatment

Use

Moisturizer for acneic skin.

Warnings

For external use only. Do not use on damaged or broken skin.

When using this product keep out of eyes. Rinse with water to remove. Stop use and ask a doctor if rash occurs, irritation and redness develop and persist for more than 72 hours.

Keep out of reach of children If swallowed, get medical help or contact a Poison Control Center right away.

Directions

• Apply to clean face at night. • Repeat use every other day for the first 15 days, then use every night. • A tingling effect may occur during application.

Additional Information

Sunburn Alert: This product contains an alpha hydroxy acid (AHA) that may increase your skin's sensitivity to the sun and particularly the possibility of sunburn. Use a sunscreen.

Inactive Ingredients

Water\Aqua\Eau, Glycolic Acid, Caprylic/Capric Triglyceride, Glycerin, Azelaic Acid, Peg-120 Methyl Glucose Dioleate, Sorbitol, Butylene Glycol, Niacinamide, Cetearyl Olivate, Cetearyl Alcohol, Cetyl Alcohol, Hexyl Laurate, Ammonium Hydroxide, Carbomer, Stearic Acid, Dimethicone, Sorbitan Olivate, Glyceryl Stearate, Peg-100 Stearate, Laureth-12, Polysilicone-11, Phenoxyethanol, Butyrospermum Parkii (Shea) Butter, Tocopheryl Acetate, Olea Europaea (Olive) Leaf Extract, Peg-30 Castor Oil, Xanthan Gum, Caprylyl Glycol, Lysolecithin, Sodium Hyaluronate, Hydrolyzed Glycosaminoglycans, Perilla Ocymoides (Beefsteak Plant) Seed Oil, Arctostaphylos Uva Ursi Leaf Extract, Disodium EDTA, Ethylhexylglycerin, Magnesium Aluminum Silicate

clarify with ACNE series

SALICYLIC ACID

SULFUR

NIACINAMIDE

AZELAIC ACID

BEAUTY CARE

Brace Beauty, Embrace Purity.

www.celesty.com

Made in TURKEY

MABA KOZMETIK A.S.

ESENTEPE MAH. YUZBASI KAYA ALDOGAN SOK.

ONUR IS MERKEZI NO:12 D:8 ISTANBUL

Distributed by CELESTY LLC

3970 NW 167TH ST. MIAMI GARDENS,

FL 33054 - USA

info@celesty.com

(FOR ACNE SKIN)

Formulated with AHAs & BHAs to exfoliate and repair acne.